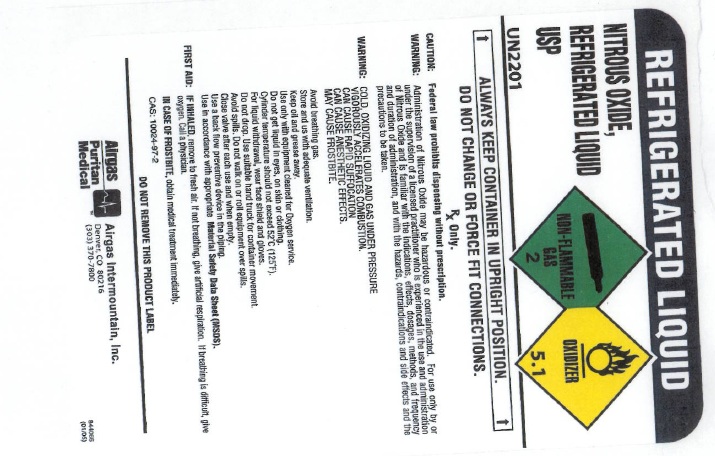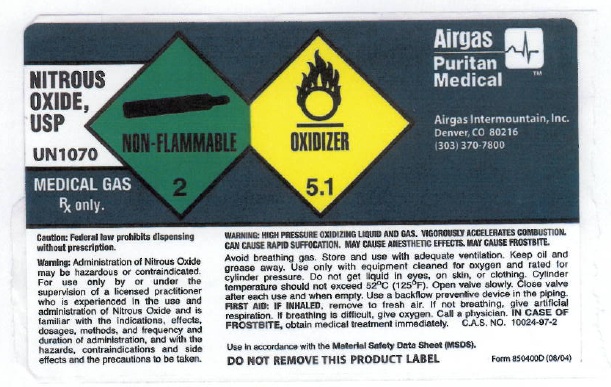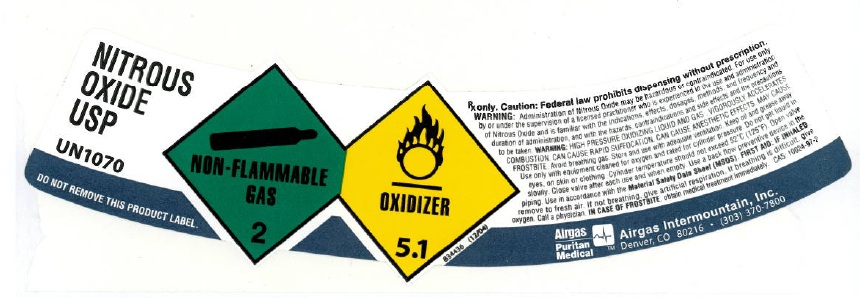 DRUG LABEL: Nitrous Oxide
NDC: 58420-003 | Form: GAS
Manufacturer: Airgas Intermountain Inc
Category: prescription | Type: HUMAN PRESCRIPTION DRUG LABEL
Date: 20100811

ACTIVE INGREDIENTS: Nitrous Oxide 992 mL/1 L

nitrous oxide

PACKAGE LABEL

REFRIGERATED LIQUID
NITROUS OXIDE, REFRIGERATED LIQUID USP UN2201
NON-FLAMMABLE GAS 2 OXIDIZER 5.1
ALWAYS KEEP CONTAINER IN UPRIGHT POSITION. DO NOT CHANGE OR FORCE FIT CONNECTIONS.
Rx only. CAUTION: Federal law prohibits dispensing without prescription.
WARNING: Administration of Nitrous Oxide may be hazardous or contraindicated. For use only by or under the supervision of a licensed practitioner who is experienced in the use and administration of Nitrous Oxide and is familiar with the indications, effects, dosages, methods, and frequency and duration of administration, and with the hazards, contraindications and side effects and the precautions to be taken.
WARNING: COLD OXIDIZING LIQUID AND GAS UNDER PRESSURE. VIGOROUSLY ACCELERATES COMBUSTION. CAN CAUSE RAPID SUFFOCATION. CAN CAUSE ANESTHETIC EFFECTS. MAY CAUSE FROSTBITE. Avoid breathing gas. Store and use with adequate ventilation. Keep oil and grease away. Use only with equipment cleaned for oxygen service and rated for cylinder pressure. Do not get liquid in eyes, on skin, or clothing. Cylinder temperature should not exceed 52C (125F). For liquid withdrawal, wear face shield and gloves. Do not drop. Use suitable hand truck for container movement. Avoid spills. Do not walk on or roll equipment over spills. Close valve after each use and when empty. Use a back flow preventive device in the piping. Use in accordance with the Material Safety Data Sheets (MSDS).
FIRST AID: IF INHALED, remove to fresh air. If not breathing, give artificial respiration. If breathing is difficult, give oxygen. Call a physician. IN CASE OF FROSTBITE, obtain medical treatment immediately.
CAS: 10024-97-2 DO NOT REMOVE THIS PRODUCT LABEL.
AIRGAS PURITAN MEDICAL Airgas Intermountain, Inc. Denver, CO 80216 (303) 370-7800
844066 (05/05)

PACKAGE LABEL

NITROUS OXIDE, USP UN1070 MEDICAL GAS Rx ONLY.
NON-FLAMMABLE GAS 2 OXIDIZER 5.1
AIRGAS PURITAN MEDICAL Airgas Intermountain, Inc. Denver, CO 80216 (303) 370-7800
CAUTION: Federal law prohibits dispensing without prescription.
WARNING: Administration of Nitrous Oxide may be hazardous or contraindicated. For use only by or under the supervision of a licensed practitioner who is experienced in the use and administration of Nitrous Oxide and is familiar with the indications, effects, dosages, methods, and frequency and duration of administration, and with the hazards, contraindications and side effects and the precautions to be taken.
WARNING: HIGH PRESSURE OXIDIZING LIQUID AND GAS. VIGOROUSLY ACCELERATES COMBUSTION. CAN CAUSE RAPID SUFFOCATION. CAN CAUSE ANESTHETIC EFFECTS. MAY CAUSE FROSTBITE. Avoid breathing gas. Store and use with adequate ventilation. Keep oil and grease away. Use only with equipment cleaned for oxygen and rated for cylinder pressure. Do not get liquid in eyes, on skin, or clothing. Cylinder temperature should not exceed 52C (125F). Open valve slowly. Close valve after each use and when empty. Use a back flow preventive device in the piping.
FIRST AID: IF INHALED, remove to fresh air. If not breathing, give artificial respiration. If breathing is difficult, give oxygen. Call a physician. IN CASE OF FROSTBITE, obtain medical treatment immediately.
CAS: 10024-97-2 Use in accordance with the Material Safety Data Sheets (MSDS).
DO NOT REMOVE THIS PRODUCT LABEL.
Form 850400D (08/04)

PACKAGE LABEL

NITROUS OXIDE USP UN1070 DO NOT REMOVE THIS PRODUCT LABEL.

NON-FLAMMABLE GAS 2OXIDIZER 5.1

834436 (12/04)

Rx only. CAUTION: Federal law prohibits dispensing without prescription.

WARNING:Administration of Nitrous Oxide may be hazardous or contraindicated. For use only by or under the supervision of a licensed practitioner who is experienced in the use and administration of Nitrous Oxide and is familiar with the indications, effects, dosages, methods, and frequency and duration of administration, and with the hazards, contraindications and side effects and the precautions to be taken.

WARNING: HIGH PRESSURE OXIDIZING LIQUID AND GAS. VIGOROUSLY ACCELERATES COMBUSTION. CAN CAUSE RAPID SUFFOCATION. CAN CAUSE ANESTHETIC EFFECTS. MAY CAUSE FROSTBITE. Avoid breathing gas. Store and use with adequate ventilation. Keep oil and grease away. Use only with equipment cleaned for oxygen and rated for cylinder pressure. Do not get liquid in eyes, on skin, or clothing. Cylinder temperature should not exceed 52C (125F). Open valve slowly. Close valve after each use and when empty. Use a back flow preventive device in the piping. Use in accordance with the Material Safety Data Sheets (MSDS).

FIRST AID: IF INHALED, remove to fresh air. If not breathing, give artificial respiration. If breathing is difficult, give oxygen. Call a physician. IN CASE OF FROSTBITE, obtain medical treatment immediately.

CAS: 10024-97-2

AIRGAS PURITAN MEDICAL Airgas Intermountain, Inc. Denver, CO 80216 (303) 370-7800